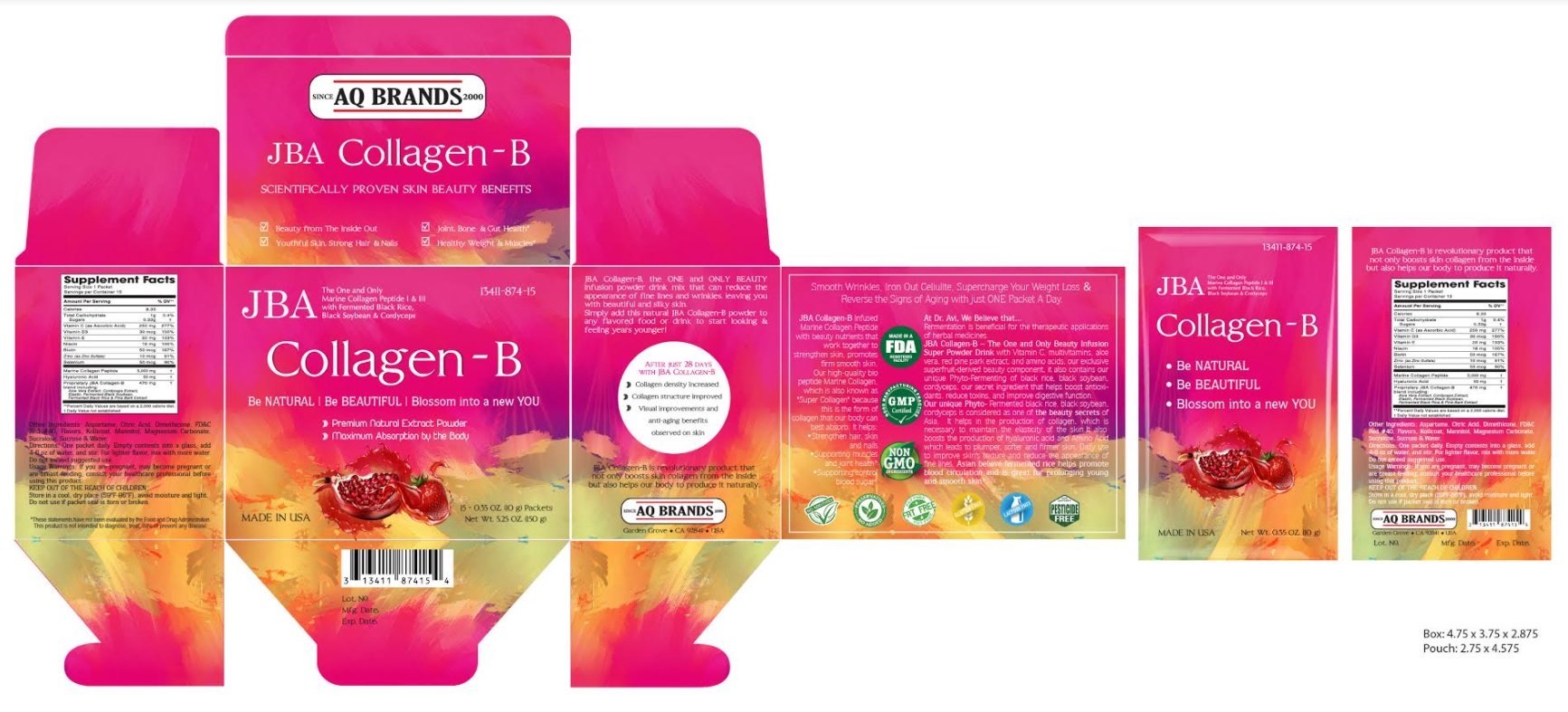 DRUG LABEL: JBA Collagen-B
NDC: 13411-874 | Form: POWDER
Manufacturer: Advanced Pharmaceutical Services, Inc. Dba Affordable Quality Pharmaceuticals
Category: other | Type: DIETARY SUPPLEMENT
Date: 20210511

ACTIVE INGREDIENTS: ASCORBIC ACID 250 mg/1 g; CHOLECALCIFEROL 30 ug/1 g; .ALPHA.-TOCOPHEROL 20 mg/1 g; NIACINAMIDE 16 mg/1 g; BIOTIN 50 ug/1 g; ZINC SULFATE 10 mg/1 g; SELENIUM 50 ug/1 g; MARINE COLLAGEN, SOLUBLE 5000 mg/1 g; HYALURONIC ACID 50 mg/1 g; ALOE VERA LEAF 100 mg/1 g; OPHIOCORDYCEPS SINENSIS 100 mg/1 g; ELASTIN BOVINE 10 mg/1 g; SOYBEAN 100 mg/1 g; RICE BRAN 100 mg/1 g; MARITIME PINE 60 mg/1 g
INACTIVE INGREDIENTS: ASPARTAME; ANHYDROUS CITRIC ACID; DIMETHICONE; FD&C RED NO. 40; KOLLICOAT SR 30D; MANNITOL; MAGNESIUM CARBONATE; SUCRALOSE; SUCROSE; WATER

Identity

DIETARY SUPPLEMENT

Warning

If you are pregnant, may become pregnant or are breast feeding, consult your healthcare professional before using this product.

Direction

One packet daily. Empty contents into a glass, add 4-6 oz of water, and stir. For lighter flavor, mix with more water.
Do not exceed suggested use.

Safe handling warning

KEEP OUT OF THE REACH OF CHILDREN.
Store in a cool, dry place (59°F-86°F), avoid moisture and light.
Do not use if packet seal is torn or broken.

Health claim

SCIENTIFICALLY PROVEN SKIN BEAUTY BENEFITS

Beauty from The Inside Out
Youthful Skin, Strong Hair & Nails
Joint, Bone & Gut Health*
Healthy Weight & Muscles*
-----------------------------------------
Be Natural - Be Beautiful - Blossom into a new YOU
- Premium Natural Extract Powder
- Maximum Absorption by the Body
-----------------------------------------
JBA Collagen-B, the ONE and ONLY BEAUTY infusion powder drink mix that can reduce the appearance of fine lines and wrinkles, leaving you with beautiful and silky skin.
Simply add this natural JBA Collagen-B powder to any flavored food or drink to start looking & feeling years younger!

After just 28 days with JBA Collagen-B
Collagen density increased
Collagen structure improved
Visual improvements and anti-aging benefits observed on skin

JBA Collagen-B is revolutionary product that not only boosts skin collagen from the inside but also helps our body to produce it naturally.
--------------------------------------------
Smooth Wrinkles, Iron Out Cellulite, Supercharge Your Weight Loss & Reverse the Signs of Aging with just ONE Packet A Day.

JBA Collagen-B Infused Marine Collagen Peptide with beauty nutrients that work together to strengthen skin, promotes firm smooth skin.

Our high-quality bio peptide Marine Collagen, which is also known as "Super Collagen" because this is the form of collagen that our body can best absorb. It helps:
•Strengthen hair, skin and nails
•Supporting muscles and joint health*
•Supporting control blood sugar*

At Dr. Avi, We Believe that...
Fermentation is beneficial for the therapeutic applications of herbal medicines.
JBA Collagen-B – The One and Only Beauty Infusion Super Powder Drink with Vitamin C, multivitamins, aloe vera, red pine park extract, and amino acids, our exclusive superfruit-derived beauty component, it also contains our unique Phyto-Fermenting of black rice, black soybean, cordyceps, our secret ingredient that helps boost antioxidants, reduce toxins, and improve digestive function.
Our unique Phyto - Fermented black rice, black soybean, cordyceps is considered as one of the beauty secrets of Asia. It helps in the production of collagen, which is necessary to maintain the elasticity of the skin. It also boosts the production of hyaluronic acid and Amino Acid which leads to plumper, softer and firmer skin. Daily use to improve skin's texture and reduce the appearance of fine lines. Asian believe fermented rice helps promote blood circulation and is great for prolonging young and smooth skin*.
* These statements have not been evaluated by the Food & Drug Administration. This product is not intended to diagnose, treat, cure, or prevent any disease.